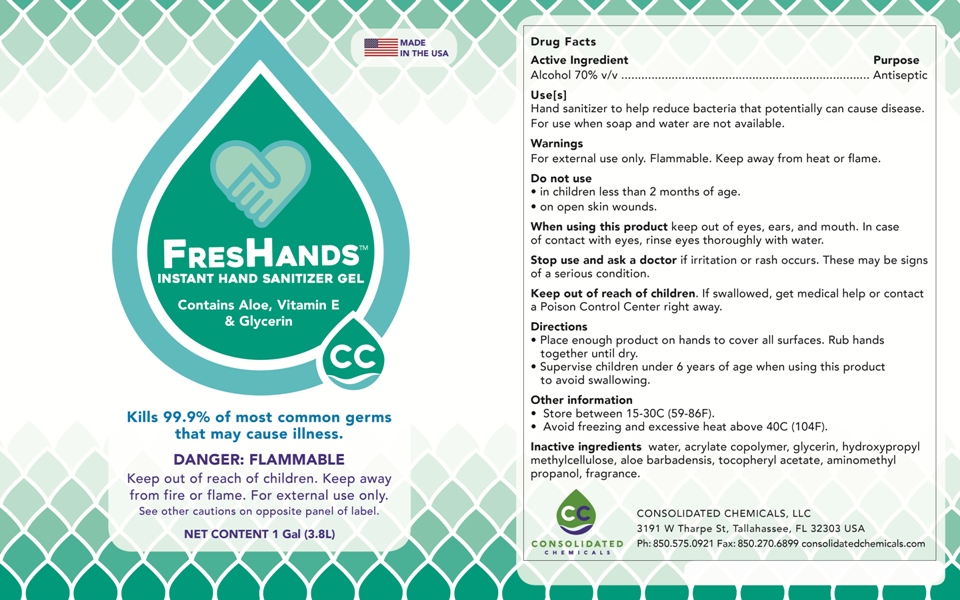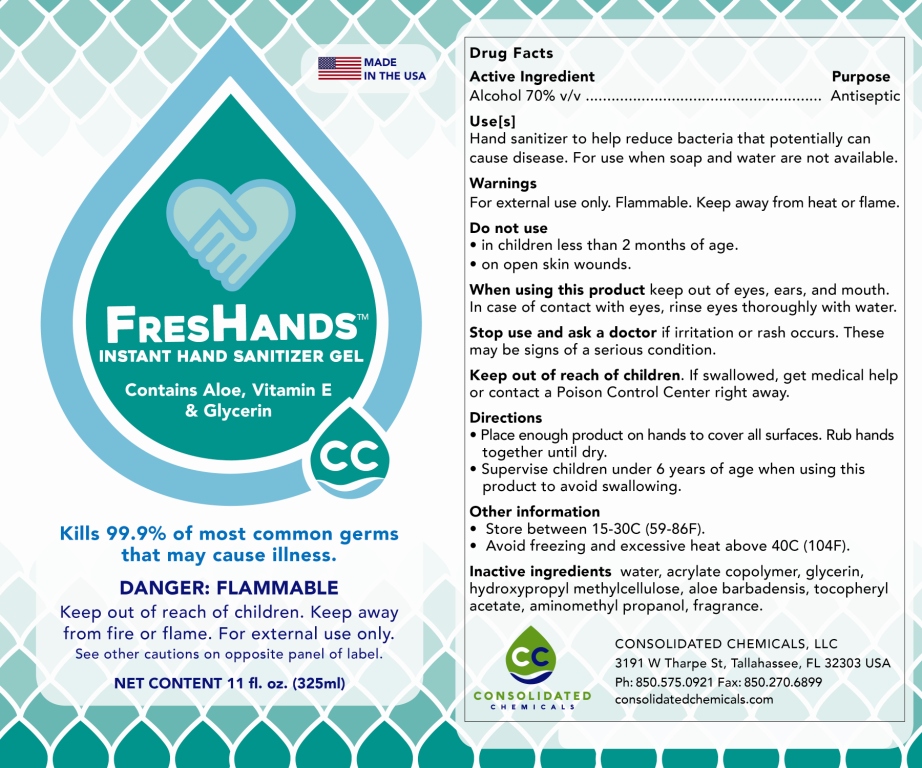 DRUG LABEL: FresHands Instant Hand Sanitizer Gel
NDC: 75632-240 | Form: GEL
Manufacturer: Consolidated Chemicals, LLC
Category: otc | Type: HUMAN OTC DRUG LABEL
Date: 20221229

ACTIVE INGREDIENTS: ALCOHOL 65 g/100 g
INACTIVE INGREDIENTS: AMINOMETHYLPROPANOL 0.065 g/100 g; .ALPHA.-TOCOPHEROL ACETATE 0.025 g/100 g; GLYCERIN 2 g/100 g; WATER; ALOE VERA LEAF 0.1 g/100 g; BUTYL ACRYLATE/METHYL METHACRYLATE/METHACRYLIC ACID COPOLYMER (18000 MW) 2.75 g/100 g; HYPROMELLOSES 0.375 g/100 g

70% Alcohol Gel Sanitizer (Acrylate & HPMC) AMP Neutralizer

This hand sanitizer is an over the counter drug product manufactured with active and inactive ingredients provided below:

Active Ingredient: Ethyl Alcohol 70% v/v

Inactive Ingredients: water, acrylate copolymer, glycerin, hydroxypropyl methylcellulose, aloe barbadensis, tocopheryl acetate, aminomethyl propanol, fragrance

Manufacturing of this hand sanitizer is consistent with 21 CFR Part 310.

Active Ingredient(s)

Alcohol 70% v/v. Purpose: Antiseptic

Purpose

Antiseptic, Hand Sanitizer

Use

Hand Sanitizer to help reduce bacteria that potentially can cause disease. For use when soap and water are not available.

Warnings

For external use only. Flammable. Keep away from heat or flame

Do not use

- in children less than 2 months of age
- on open skin wounds

When using this product keep out of eyes, ears, and mouth. In case of contact with eyes, rinse eyes thoroughly with water.
Stop use and ask a doctor if irritation or rash occurs. These may be signs of a serious condition.
Keep out of reach of children. If swallowed, get medical help or contact a Poison Control Center right away.

Stop use and ask a doctor if irritation or rash occurs. These may be signs of a serious condition.

Keep out of reach of children. If swallowed, get medical help or contact a Poison Control Center right away.

Directions

- Place enough product on hands to cover all surfaces. Rub hands together until dry.
- Supervise children under 6 years of age when using this product to avoid swallowing.

Other information

- Store between 15-30C (59-86F)
- Avoid freezing and excessive heat above 40C (104F)

Inactive ingredients

water, acrylate copolymer, glycerin, hydroxypropyl methylcellulose, aloe barbadensis, tocopheryl acetate, aminomethyl propanol, fragrance

Package Label - Principal Display Panel

1 Gal NDC: 75632-240-40